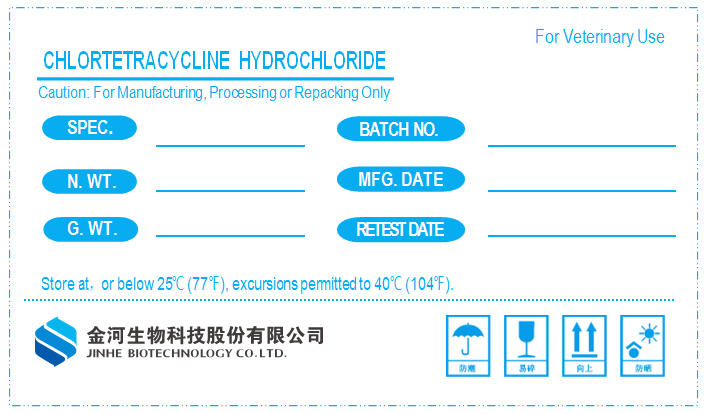 DRUG LABEL: Chlortetracycline Hydrochloride
NDC: 66623-005 | Form: POWDER
Manufacturer: Jinhe Biotechnology Co., Ltd.
Category: other | Type: BULK INGREDIENT - ANIMAL DRUG
Date: 20191127

ACTIVE INGREDIENTS: Chlortetracycline Hydrochloride 1 kg/1 kg

CHLORTETRACYCLINE HYDROCHLORIDE

PRINCIPAL DISPLAY PANEL - Shipping Label

For Veterinary Use

CHLORTETRACYCLINE HYDROCHLORIDE
Caution: For Manufacturing, Processing or Repacking Only

SPEC.

BATCH NO.

N. WT.

MFG. DATE

G. WT.

RETEST DATE

Store at, or below 25°C (77°F), excursions permitted to 40°C (104°F).

JINHE BIOTECHNOLOGY CO.LTD.